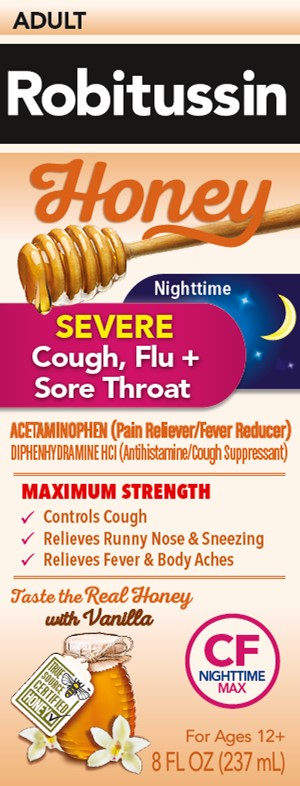 DRUG LABEL: Robitussin Honey Severe Cough, Flu Plus Sore Throat Nighttime
NDC: 0031-8770 | Form: SOLUTION
Manufacturer: Haleon US Holdings LLC
Category: otc | Type: HUMAN OTC DRUG LABEL
Date: 20240426

ACTIVE INGREDIENTS: ACETAMINOPHEN 650 mg/20 mL; DIPHENHYDRAMINE HYDROCHLORIDE 25 mg/20 mL
INACTIVE INGREDIENTS: ANHYDROUS CITRIC ACID; CARBOXYMETHYLCELLULOSE SODIUM, UNSPECIFIED; GLYCERIN; HONEY; POLYETHYLENE GLYCOL, UNSPECIFIED; PROPYLENE GLYCOL; WATER; SODIUM BENZOATE; SODIUM CITRATE, UNSPECIFIED FORM; SODIUM GLUCONATE; SUCRALOSE; XANTHAN GUM

Drug Facts

Active ingredients (in each 20 mL)

Acetaminophen 650 mg

Diphenhydramine HCl 25 mg

Purpose

Pain reliever/Fever reducer

Antihistamine/Cough suppressant

Uses

- temporarily relieves these symptoms occurring with a cold or flu, hay fever, or other upper respiratory allergies:
  - cough due to minor throat and bronchial irritation
  - minor aches and pains
  - sore throat pain
  - headache
  - runny nose, sneezing, itchy watery eyes
  - itching of the nose and throat
- temporarily relieves your cough to help you sleep
- temporarily reduces fever

Warnings

Liver warning:

This product contains acetaminophen.

Severe liver damage may occur if you take

- more than 6 doses in any 24-hour period, which is the maximum daily amount
- with other drugs containing acetaminophen
- 3 or more alcoholic drinks every day while using this product

Allergy alert: acetaminophen may cause severe skin reactions. Symptoms may include:

- skin reddening
- blisters
- rash

If a skin reaction occurs, stop use and seek medical help right away.

Sore throat warning

If sore throat is severe, persists for more than 2 days, is accompanied or followed by fever, headache, rash, nausea, or vomiting, consult a doctor promptly.

Do not use

- to sedate a child or to make a child sleepy
- with any other drug containing acetaminophen (prescription or nonprescription). If you are not sure whether a drug contains acetaminophen, ask a doctor or pharmacist.
- with any other product containing diphenhydramine, even one used on skin

Ask a doctor before use if you have

- liver disease
- cough that occurs with too much phlegm (mucus)
- a breathing problem or chronic cough that lasts or as occurs with smoking, asthma, emphysema or chronic bronchitis
- if you have glaucoma or difficulty in urination due to enlargement of prostate gland

Ask a doctor or pharmacist before use if you are

- taking sedatives or tranquilizers
- taking the blood thinning drug warfarin
- taking any other pain reliever/fever reducer

When using this product

- do not use more than directed
- marked drowsiness may occur
- avoid alcoholic drinks
- alcohol, sedatives, and tranquilizers may increase drowsiness
- be careful when driving a motor vehicle or operating machinery
- excitability may occur, especially in children

Stop use and ask a doctor if

- pain or cough gets worse or lasts more than 7 days
- fever gets worse or lasts more than 3 days
- redness or swelling is present
- new symptoms occur
- cough comes back or occurs with rash or headache that lasts. These could be signs of a serious condition.

PREGNANCY OR BREAST FEEDING

If pregnant or breast-feeding, ask a health professional before use.

Keep out of reach of children. In case of overdose, get medical help or contact a Poison Control Center right away. Prompt medical attention is critical for adults as well as for children, even if you do not notice any signs or symptoms.

Directions

- do not take more than 6 doses in any 24-hour period
- do not exceed recommended dosage. Taking more than the recommended dose (overdose) may cause serious liver damage.
- measure only with dosing cup provided
- keep dosing cup with product
- mL = milliliter
- this adult product is not intended for use in children under 12 years of age

Age | dose
adults and children; 12 years and over | 20 mL every 4 hours
children under 12 years | do not use

Other information

- each 20 mL contains: sodium 22 mg
- store at 20-25°C (68-77°F). Do not refrigerate.

Inactive ingredients

anhydrous citric acid, carboxymethylcellulose sodium, glycerin, natural & artificial flavors, natural grade A honey, polyethylene glycol, propylene glycol, purified water, sodium benzoate, sodium citrate, sodium gluconate, sucralose, xanthan gum

Questions or comments?

call weekdays from 8 AM to 6 PM EST at 1-800-245-1040

Additional information

Packaged with Tamper-Evident bottle cap. Do Not Use if breakable ring is separated or missing.

Distributed by: Haleon, Warren, NJ 07059

For most recent product information, visit www.robitussin.com

Trademarks owned or licensed by Haleon.

©2023 Haleon or licensor.

Pat. Info www.productpats.com

Made in Canada

PRINCIPAL DISPLAY PANEL

ADULT
Robitussin

Honey

Nighttime

SEVERE
Cough, Flu +
Sore Throat

ACETAMINOPHEN (Pain Reliever/Fever Reducer)
DIPHENHYDRAMINE HCl (Antihistamine/Cough Suppressant)

MAXIMUM STRENGTH

✓ Controls Cough
✓ Relieves Runny Nose & Sneezing
✓ Relieves Fever & Body Aches

Taste the Real Honey
with Vanilla

CF
NIGHTTIME
MAX

For Ages 12+

8 FL OZ (237 mL)